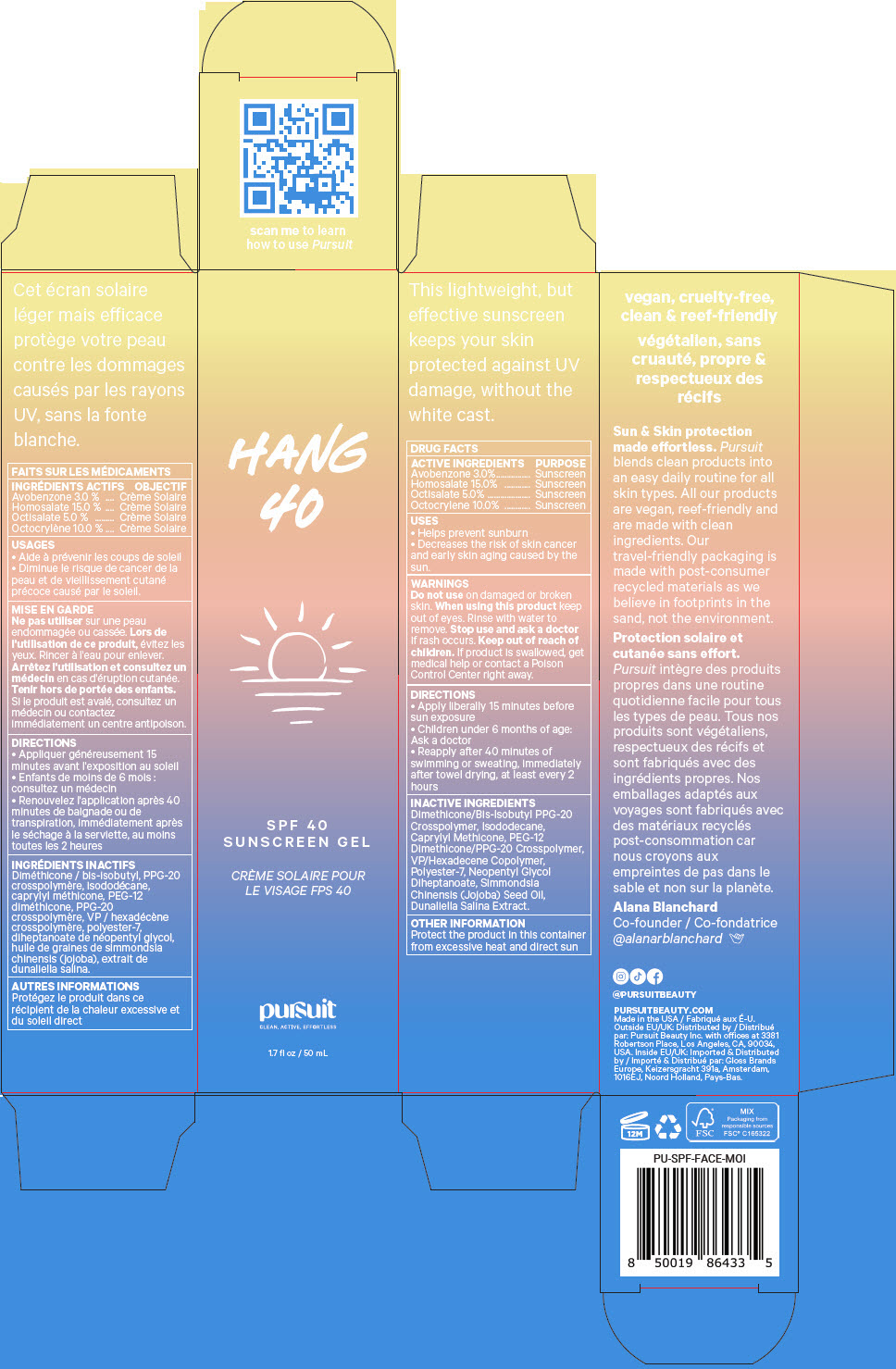 DRUG LABEL: Pursuit Hang 40 SPF 40 Sunscreen
NDC: 83040-003 | Form: GEL
Manufacturer: Pursuit Beauty Inc.
Category: otc | Type: HUMAN OTC DRUG LABEL
Date: 20221205

ACTIVE INGREDIENTS: AVOBENZONE 3 g/100 mL; HOMOSALATE 15 g/100 mL; OCTISALATE 5 g/100 mL; OCTOCRYLENE 10 g/100 mL
INACTIVE INGREDIENTS: DIMETHICONE/BIS-ISOBUTYL PPG-20 CROSSPOLYMER 20 g/100 mL; ISODODECANE 20 g/100 mL; CAPRYLYL TRISILOXANE 11.4995 g/100 mL; PEG-12 DIMETHICONE/PPG-20 CROSSPOLYMER 11.4995 g/100 mL; VINYLPYRROLIDONE/HEXADECENE COPOLYMER 2 g/100 mL; POLYESTER-7 1.1 g/100 mL; NEOPENTYL GLYCOL DIHEPTANOATE 0.9 g/100 mL; JOJOBA OIL 0.0009998 g/100 mL; DUNALIELLA SALINA 2E-07 g/100 mL

Pursuit Hang 40 SPF 40 Sunscreen Gel

DRUG FACTS

ACTIVE INGREDIENT

ACTIVE INGREDIENTS | PURPOSE
Avobenzone 3.0% | Sunscreen
Homosalate 15.0% | Sunscreen
Octisalate 5.0% | Sunscreen
Octocrylene 10.0% | Sunscreen

USES

- Helps prevent sunburn
- Decreases the risk of skin cancer and early skin aging caused by the sun.

WARNINGS

Do not use on damaged or broken skin. When using this product keep out of eyes. Rinse with water to remove. Stop use and ask a doctor if rash occurs.

Keep out of reach of children. If product is swallowed, get medical help or contact a Poison Control Center right away.

DIRECTIONS

- Apply liberally 15 minutes before sun exposure
- Children under 6 months of age: Ask a doctor
- Reapply after 40 minutes of swimming or sweating, immediately after towel drying, at least every 2 hours

INACTIVE INGREDIENTS

Dimethicone/Bis-Isobutyl PPG-20 Crosspolymer, Isododecane, Caprylyl Methicone, PEG-12 Dimethicone/PPG-20 Crosspolymer, VP/Hexadecene Copolymer, Polyester-7, Neopentyl Glycol Diheptanoate, Simmondsia Chinensis (Jojoba) Seed Oil, Dunaliella Salina Extract.

OTHER INFORMATION

Protect the product in this container from excessive heat and direct sun

Distributed by: Pursuit Beauty Inc. with offices at 3381 Robertson Place, Los Angeles, CA, 90034, USA.

Imported & Distributed by: Gloss Brands Europe, Keizersgracht 391a, Amsterdam, 1016EJ, Noord Holland, Pays-Bas.

PRINCIPAL DISPLAY PANEL - 50 mL Tube Carton

HANG
40

SPF 40
SUNSCREEN GEL

pursuit

CLEAN, ACTIVE, EFFORTLESS

1.7 fl oz / 50 mL